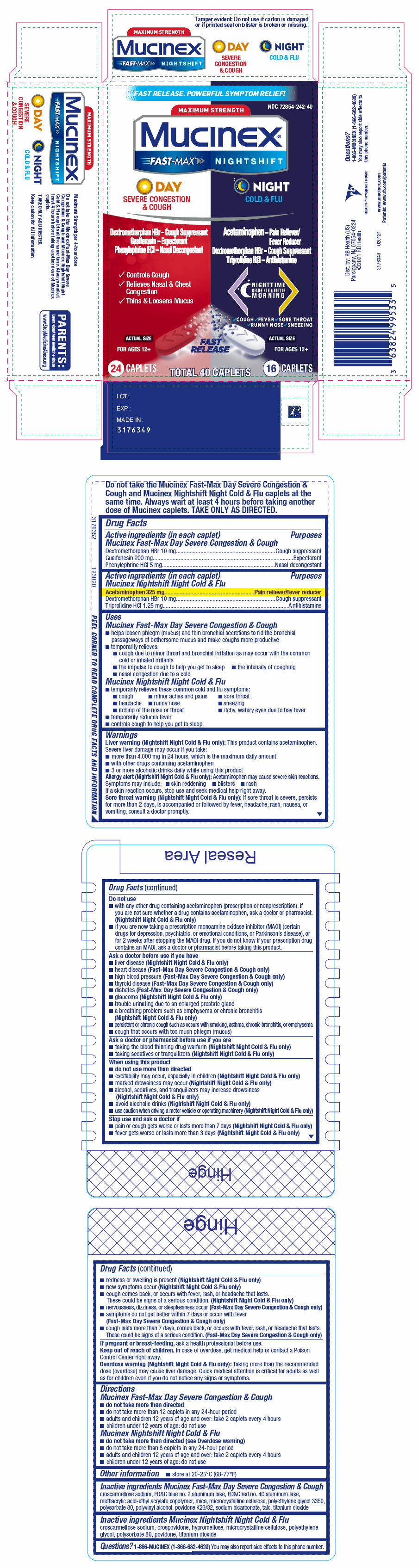 DRUG LABEL: Mucinex Fast-Max Day Severe Congestion and Cough and Mucinex Nightshift Night Cold and Flu
NDC: 72854-242 | Form: KIT | Route: ORAL
Manufacturer: RB Health (US) LLC
Category: otc | Type: HUMAN OTC DRUG LABEL
Date: 20241223

ACTIVE INGREDIENTS: DEXTROMETHORPHAN HYDROBROMIDE 10 mg/1 1; GUAIFENESIN 200 mg/1 1; PHENYLEPHRINE HYDROCHLORIDE 5 mg/1 1; DEXTROMETHORPHAN HYDROBROMIDE 10 mg/1 1; TRIPROLIDINE HYDROCHLORIDE 1.25 mg/1 1; ACETAMINOPHEN 325 mg/1 1
INACTIVE INGREDIENTS: CROSCARMELLOSE SODIUM; FD&C BLUE NO. 2; FD&C RED NO. 40; ALUMINUM OXIDE; MICA; MICROCRYSTALLINE CELLULOSE; POLYETHYLENE GLYCOL, UNSPECIFIED; POLYSORBATE 80; POLYVINYL ALCOHOL, UNSPECIFIED; POVIDONE, UNSPECIFIED; SODIUM BICARBONATE; TALC; TITANIUM DIOXIDE; CROSCARMELLOSE SODIUM; CROSPOVIDONE; HYPROMELLOSE, UNSPECIFIED; MICROCRYSTALLINE CELLULOSE; POLYETHYLENE GLYCOL, UNSPECIFIED; POLYSORBATE 80; POVIDONE, UNSPECIFIED; TITANIUM DIOXIDE

Mucinex® Fast-Max® Day Severe Congestion & Cough and Mucinex Nightshift Night Cold & Flu
Maximum Strength

Drug Facts

ACTIVE INGREDIENT

PURPOSE

Active ingredients (in each caplet) Mucinex Fast-Max Day Severe Congestion & Cough | Purposes
Dextromethorphan HBr 10 mg | Cough suppressant
Guaifenesin 200 mg | Expectorant
Phenylephrine HCl 5 mg | Nasal decongestant

Active ingredients (in each caplet) Mucinex Nightshift Night Cold & Flu | Purposes
Acetaminophen 325 mg | Pain reliever/fever reducer
Dextromethorphan HBr 10 mg | Cough suppressant
Triprolidine HCl 1.25 mg | Antihistamine

Uses

Mucinex Fast-Max Day Severe Congestion & Cough

- helps loosen phlegm (mucus) and thin bronchial secretions to rid the bronchial passageways of bothersome mucus and make coughs more productive
- temporarily relieves:
  - cough due to minor throat and bronchial irritation as may occur with the common cold or inhaled irritants
  - the impulse to cough to help you get to sleep
  - the intensity of coughing
  - nasal congestion due to a cold

Mucinex Nightshift Night Cold & Flu

- temporarily relieves these common cold and flu symptoms:
  - cough
  - minor aches and pains
  - sore throat
  - headache
  - runny nose
  - sneezing
  - itching of the nose or throat
  - itchy, watery eyes due to hay fever
- temporarily reduces fever
- controls cough to help you get to sleep

Warnings

Liver warning (Nightshift Night Cold & Flu only)

This product contains acetaminophen. Severe liver damage may occur if you take:

- more than 4,000 mg in 24 hours, which is the maximum daily amount
- with other drugs containing acetaminophen
- 3 or more alcoholic drinks daily while using this product

Allergy alert (Nightshift Night Cold & Flu only)

Acetaminophen may cause severe skin reactions. Symptoms may include:

- skin reddening
- blisters
- rash

If a skin reaction occurs, stop use and seek medical help right away.

Sore throat warning (Nightshift Night Cold & Flu only)

If sore throat is severe, persists for more than 2 days, is accompanied or followed by fever, headache, rash, nausea, or vomiting, consult a doctor promptly.

Do not use

- with any other drug containing acetaminophen (prescription or nonprescription). If you are not sure whether a drug contains acetaminophen, ask a doctor or pharmacist. (Nightshift Night Cold & Flu only)
- if you are now taking a prescription monoamine oxidase inhibitor (MAOI) (certain drugs for depression, psychiatric, or emotional conditions, or Parkinson's disease), or for 2 weeks after stopping the MAOI drug. If you do not know if your prescription drug contains an MAOI, ask a doctor or pharmacist before taking this product.

Ask a doctor before use if you have

- liver disease (Nightshift Night Cold & Flu only)
- heart disease (Fast-Max Day Severe Congestion & Cough only)
- high blood pressure (Fast-Max Day Severe Congestion & Cough only)
- thyroid disease (Fast-Max Day Severe Congestion & Cough only)
- diabetes (Fast-Max Day Severe Congestion & Cough only)
- glaucoma (Nightshift Night Cold & Flu only)
- trouble urinating due to an enlarged prostate gland
- a breathing problem such as emphysema or chronic bronchitis (Nightshift Night Cold & Flu only)
- persistent or chronic cough such as occurs with smoking, asthma, chronic bronchitis, or emphysema
- cough that occurs with too much phlegm (mucus)

Ask a doctor or pharmacist before use if you are

- taking the blood thinning drug warfarin (Nightshift Night Cold & Flu only)
- taking sedatives or tranquilizers (Nightshift Night Cold & Flu only)

When using this product

- do not use more than directed
- excitability may occur, especially in children (Nightshift Night Cold & Flu only)
- marked drowsiness may occur (Nightshift Night Cold & Flu only)
- alcohol, sedatives, and tranquilizers may increase drowsiness (Nightshift Night Cold & Flu only)
- avoid alcoholic drinks (Nightshift Night Cold & Flu only)
- use caution when driving a motor vehicle or operating machinery (Nightshift Night Cold & Flu only)

Stop use and ask a doctor if

- pain or cough gets worse or lasts more than 7 days (Nightshift Night Cold & Flu only)
- fever gets worse or lasts more than 3 days (Nightshift Night Cold & Flu only)
- redness or swelling is present (Nightshift Night Cold & Flu only)
- new symptoms occur (Nightshift Night Cold & Flu only)
- cough comes back, or occurs with fever, rash, or headache that lasts. These could be signs of a serious condition. (Nightshift Night Cold & Flu only)
- nervousness, dizziness, or sleeplessness occur (Fast-Max Day Severe Congestion & Cough only)
- symptoms do not get better within 7 days or occur with fever (Fast-Max Day Severe Congestion & Cough only)
- cough lasts more than 7 days, comes back, or occurs with fever, rash, or headache that lasts. These could be signs of a serious condition. (Fast-Max Day Severe Congestion & Cough only)

PREGNANCY OR BREAST FEEDING

If pregnant or breast-feeding, ask a health professional before use.

Keep out of reach of children. In case of overdose, get medical help or contact a Poison Control Center right away.

Overdose warning (Nightshift Night Cold & Flu only)

Taking more than the recommended dose (overdose) may cause liver damage. Quick medical attention is critical for adults as well as for children even if you do not notice any signs or symptoms.

Directions

Mucinex Fast-Max Day Severe Congestion & Cough

- do not take more than directed
- do not take more than 12 caplets in any 24-hour period
- adults and children 12 years of age and over: take 2 caplets every 4 hours
- children under 12 years of age: do not use

Mucinex Nightshift Night Cold & Flu

- do not take more than directed (see Overdose warning)
- do not take more than 8 caplets in any 24-hour period
- adults and children 12 years of age and over: take 2 caplets every 4 hours
- children under 12 years of age: do not use

Other information

- store at 20-25°C (68-77°F)

Inactive ingredients Mucinex Fast-Max Day Severe Congestion & Cough

croscarmellose sodium, FD&C blue no. 2 aluminum lake, FD&C red no. 40 aluminum lake, methacrylic acid-ethyl acrylate copolymer, mica, microcrystalline cellulose, polyethylene glycol 3350, polysorbate 80, polyvinyl alcohol, povidone K29/32, sodium bicarbonate, talc, titanium dioxide

Inactive ingredients Mucinex Nightshift Night Cold & Flu

croscarmellose sodium, crospovidone, hypromellose, microcrystalline cellulose, polyethylene glycol, polysorbate 80, povidone, titanium dioxide

Questions?

1-866-MUCINEX (1-866-682-4639) You may also report side effects to this phone number.

Dist. by: RB Health (US)
Parsippany, NJ 07054-0224

PRINCIPAL DISPLAY PANEL - Kit Carton

FAST RELEASE. POWERFUL SYMPTOM RELIEF!

NDC 72854-242-40

MAXIMUM STRENGTH
Mucinex®
FAST-MAX® NIGHTSHIFT

DAY
SEVERE CONGESTION
& COUGH

Dextromethorphan HBr – Cough Suppressant
Guaifenesin – Expectorant
Phenylephrine HCl – Nasal Decongestant

- Controls Cough
- Relieves Nasal & Chest
  Congestion
- Thins & Loosens Mucus

ACTUAL SIZE

FOR AGES 12+

24 CAPLETS

NIGHT
COLD & FLU

Acetaminophen – Pain Reliever/
Fever Reducer
Dextromethorphan HBr – Cough Suppressant
Triprolidine HCl – Antihistamine

NIGHTTIME
RELIEF FOR A BETTER
MORNING

✓COUGH ✓FEVER ✓SORE THROAT
✓RUNNY NOSE ✓SNEEZING

ACTUAL SIZE

FOR AGES 12+

16 CAPLETS

FAST
RELEASE

TOTAL 40 CAPLETS